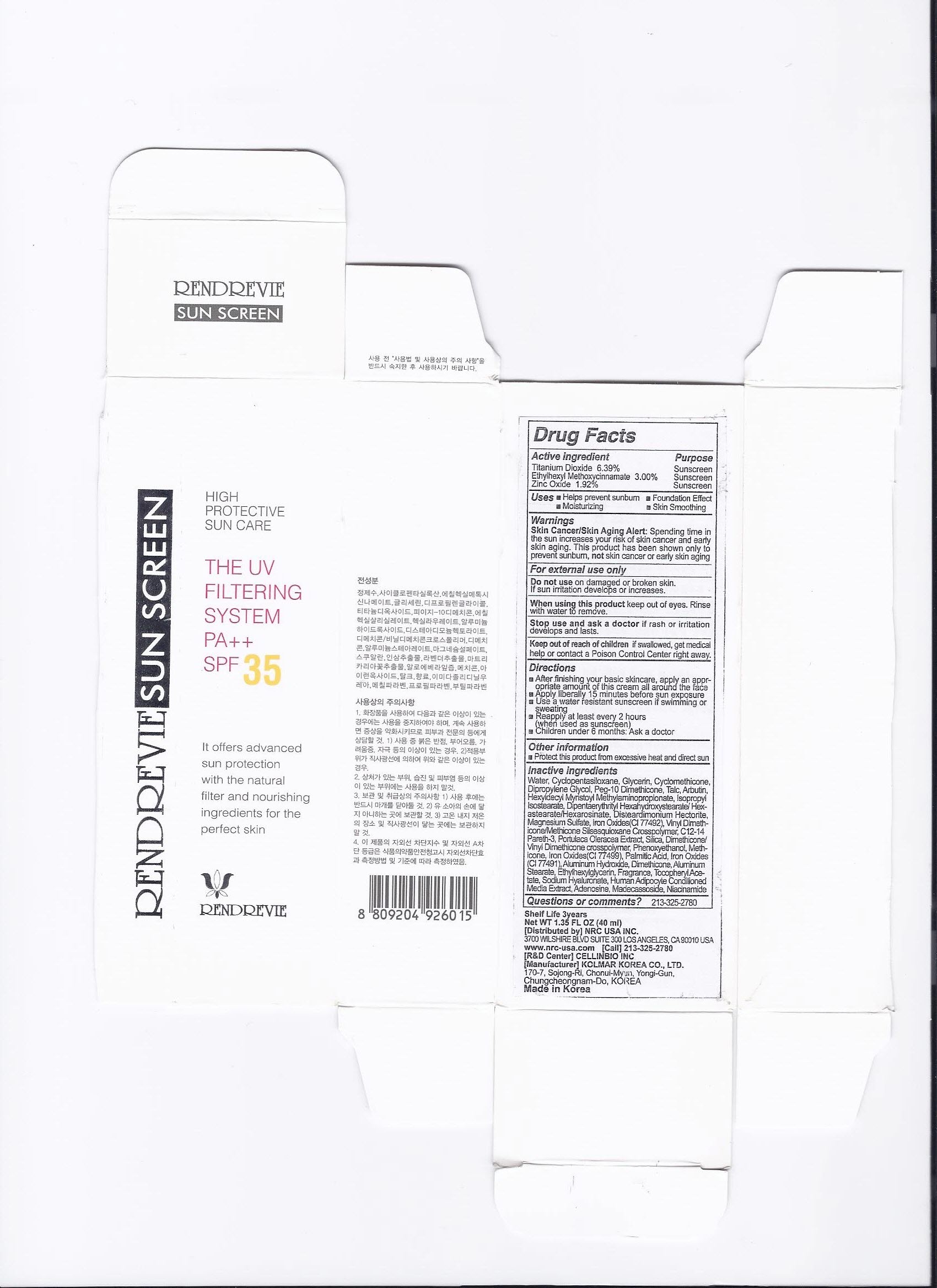 DRUG LABEL: Rendrevie Sun Screen SPF35 PA
NDC: 76173-1001 | Form: CREAM
Manufacturer: Cellinbio Co Ltd
Category: otc | Type: HUMAN OTC DRUG LABEL
Date: 20110720

ACTIVE INGREDIENTS: OCTINOXATE 5.625 mL/75 mL; TITANIUM DIOXIDE 3.89 mL/75 mL; OCTISALATE 2.25 mL/75 mL
INACTIVE INGREDIENTS: WATER; CYCLOMETHICONE 5; GLYCERIN; DIPROPYLENE GLYCOL; HEXYL LAURATE; TALC; DIMETHICONE; DISTEARYLDIMONIUM CHLORIDE; MAGNESIUM SULFATE ANHYDROUS; ALGELDRATE; ALUMINUM STEARATE; IMIDUREA; METHYLPARABEN; PROPYLPARABEN; ALOE VERA LEAF; CHAMOMILE; LAVANDULA ANGUSTIFOLIA FLOWER; ASIAN GINSENG; SQUALANE; FERRIC OXIDE YELLOW; BUTYLPARABEN; FERRIC OXIDE RED; FERROSOFERRIC OXIDE

Rendrevie Sun Screen SPF35 PA++

Drug Facts

Active ingredient

Octinoxate 7.50%
Titanium Dioxide 5.19%
Octisalate 3.00%

Purpose

Sunscreen

Keep out of Reach of Children

If swallowed, get medical help or contact a Posion Control Center right away.

Indication & Usage

Directions
Apply liberally 15 minutes before sun exposure
Use a water resistant sunscreen if swimming or sweating
Reapply at least every 2 hours
Children under 6 months: Ask a doctor

Warnings

Skin Cancer/Skin Aging Alert: Spending time in the sun increases your risk of skin cancer and early skin aging. This product has been shown only to prevent sunburn, not skin cancer or early skin aging

For extenal use only

Do not use on damaged or broken skin

When using this product keep out of eyes. Rinse with water to remove.

Stop use and ask a doctor if rash occurs.

Dosage & Administration

Helps prevent sunburn

Inactive Ingredient

Water, Cyclopentasiloxane, Glycerin, Dipropylene Glycol, Peg-10 Dimethicone, Hexyl Laurate, Talc, Dimethicone, Dimethicone/Vinyl Dimethicone Crosspolymer, Disteardimonium Hectorite, Magnesium Sulfate, Aluminum Hydroxide, Aluminum Stearate, Fragrance, Imidazolidinyl Urea, Methylparaben, Propylparaben, Aloe Barbadensis Leaf Juice, Chamomilla Recutita(Matricaria) Flower Extract, Lavandula Angustifolia(Lavender) Extract, Panax Ginseng Root Extract, Squalane, Iron Oxides(CI 77492, CI 77491, CI 77499), Butylparaben, Methicone

Rendrevie Sun Screen SPF35 PA++

NRC Rendrevie sun sunscreen SPF35 PA++

Net WT. 2.54FL OZ(75ml)